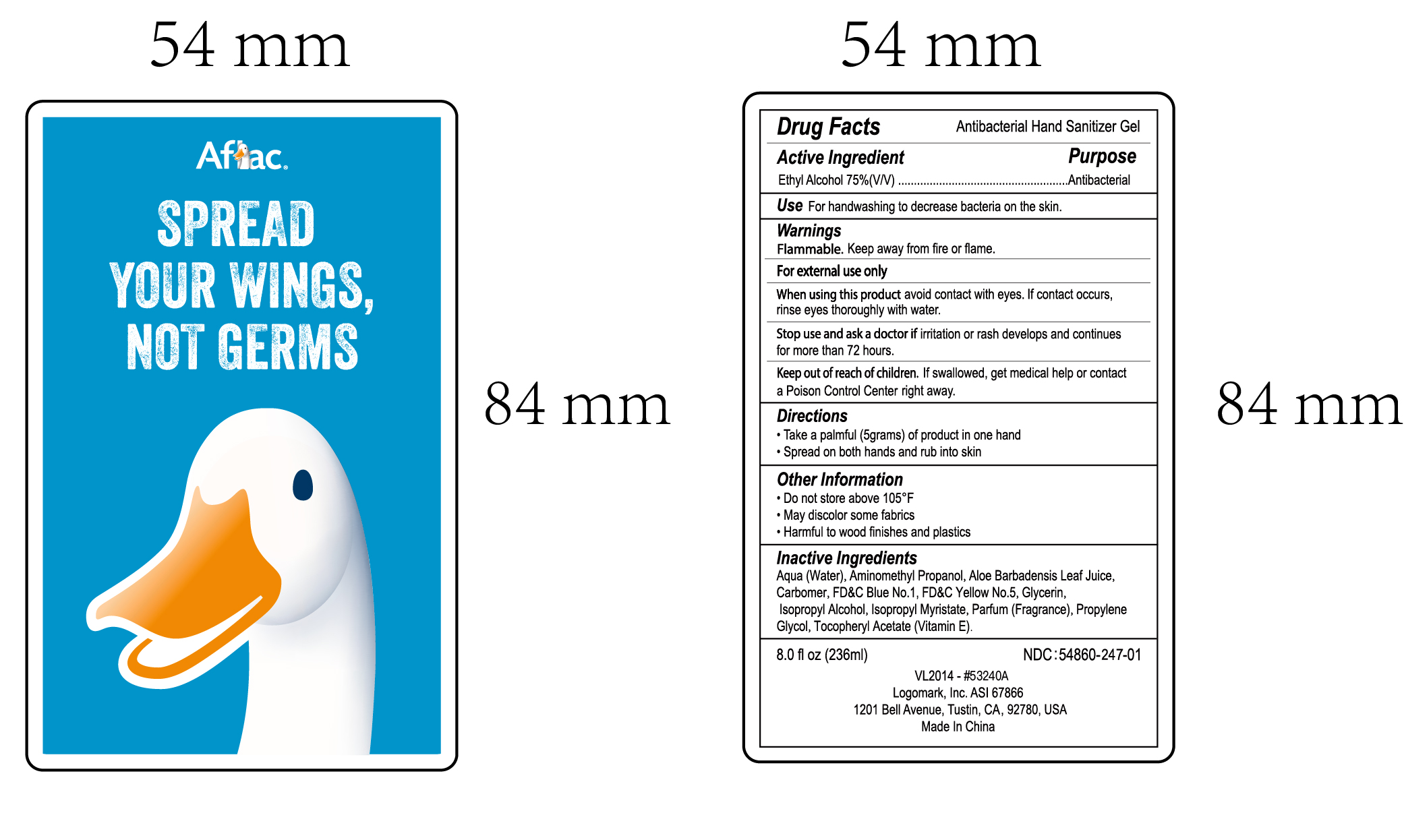 DRUG LABEL: Aflac hand sanitizer 236ml
NDC: 54860-247 | Form: LIQUID
Manufacturer: Shenzhen Lantern Science Co.,Ltd
Category: otc | Type: HUMAN OTC DRUG LABEL
Date: 20200511

ACTIVE INGREDIENTS: ALCOHOL 75 mL/100 mL
INACTIVE INGREDIENTS: ALOE VERA LEAF 0.1 mL/100 mL; ALOE 0.2 mL/100 mL; ISOPROPYL MYRISTATE 0.001 mL/100 mL; CARBOMER 940 0.4 mL/100 mL; WATER 23.057972 mL/100 mL; ISOPROPYL ALCOHOL 0.5 mL/100 mL; FD&C YELLOW NO. 5 0.00002 mL/100 mL; AMINOMETHYLPROPANOL 0.14 mL/100 mL; FD&C BLUE NO. 1 0.000008 mL/100 mL; GLYCERIN 0.5 mL/100 mL; PROPYLENE GLYCOL 0.1 mL/100 mL; .ALPHA.-TOCOPHEROL ACETATE 0.001 mL/100 mL

Aflac hand sanitizer 236ml

Active Ingredient

Medicinal Ingredients Purpose

Ethyl Alcoh75% v/v Antibacterial

Warning

Flammable,keep away from fire or flame.

For external use only.

WARNINGS AND PRECAUTIONS

For external use only.

Flammable, keep away from heat and flame.

STOP USE

Discontinue if skin becomes irritated and ask a doctor .

Keep out of reach of children. In case of accidental ingestion, seek professional assistance or contact a poson control center immediately.

Inactive ingredients

water，Isopropyl Alcohol，Glycerin，Carbomer，Aminomethyl Propanol，Parfum，Propylene Glycol，ISOPROPYL MYRISTATE，ALOE BARBADENSIS LEAF JUICE，Tocopheryl Acetate，FD&C Yellow No.5(Tartrazine),FD&C Blue No.1.

USE

For handwashing to decrease bacteria on the skin.

When using this product

Avoid contact with eyes,if contact occurs,rinse eyes thoroughly with water.

Stop use and ask a doctor

if irritation or rash develops and continues for more than 72 hours.

OTHER SAFETY INFORMATION

Do not store above105℉

May discolor some fabrics.

Harmful to wood finishes and plastics.

Directions

Take a palmful(5grams) of product in one hand

Spread on both hands and rub into skin

Directions

Take a palmful(5grams) of product in one hand

Spread on both hands and rub into skin